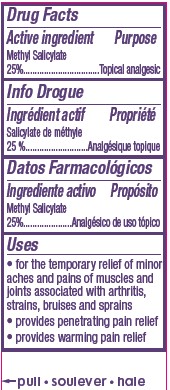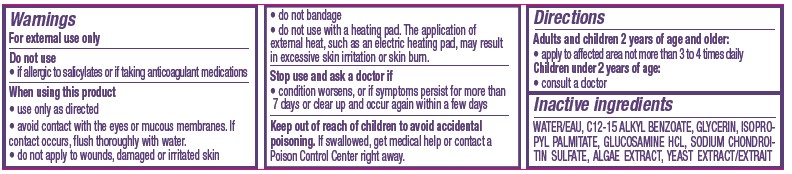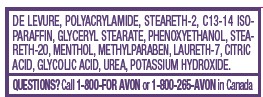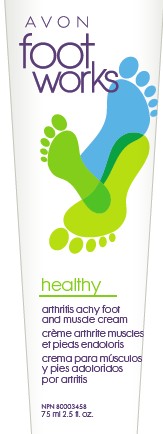 DRUG LABEL: foot works
NDC: 10096-0004 | Form: CREAM
Manufacturer: New Avon LLC
Category: otc | Type: HUMAN OTC DRUG LABEL
Date: 20190101

ACTIVE INGREDIENTS: METHYL SALICYLATE	 250 mg/1 mL
INACTIVE INGREDIENTS: WATER

Footworks Arthritis Achy Foot and Muscle Cream

Active ingredient
Methyl Salicylate
25%................

Purpose
..................Topical analgesic

Uses
• for the temporary relief of minor aches and pains of muscles and joints associated with arthritis, strains, bruises and sprains
• provides penetrating pain relief
• provides warming pain relief

Warnings
For external use only

Do not use
• if allergic to salicylates or if taking anticoagulant medications

When using this product
• use only as directed
• avoid contact with the eyes or mucous membranes. If contact occurs, flush thoroughly with water.
• do not apply to wounds, damaged or irritated skin
• do not bandage
• do not use with a heating pad. The application of external heat, such as an electric heating pad, may result in excessive skin irritation or skin burn.

Stop use and ask a doctor if
• condition worsens, or if symptoms persist for more than 7 days or clear up and occur again within a few days

Keep out of reach of children to avoid accidental poisoning. If swallowed, get medical help or contact a Poison Control Center right away.

Directions
Adults and children 2 years of age and older:
• apply to affected area not more than 3 to 4 times daily
Children under 2 years of age:
• consult a doctor

Inactive ingredients
WATER/EAU, C12-15 ALKYL BENZOATE, GLYCERIN, ISOPROPYL PALMITATE, GLUCOSAMINE HCL, SODIUM CHONDROITIN SULFATE, ALGAE EXTRACT, YEAST EXTRACT/EXTRAIT DE LEVURE, POLYACRYLAMIDE, STEARETH-2, C13-14 ISOPARAFFIN, GLYCERYL STEARATE, PHENOXYETHANOL, STEARETH- 20, MENTHOL, METHYLPARABEN, LAURETH-7, CITRIC ACID, GLYCOLIC ACID, UREA, POTASSIUM HYDROXIDE.

QUESTIONS

QUESTIONS? Call 1-800-FOR AVON or 1-800-265-AVON in Canada